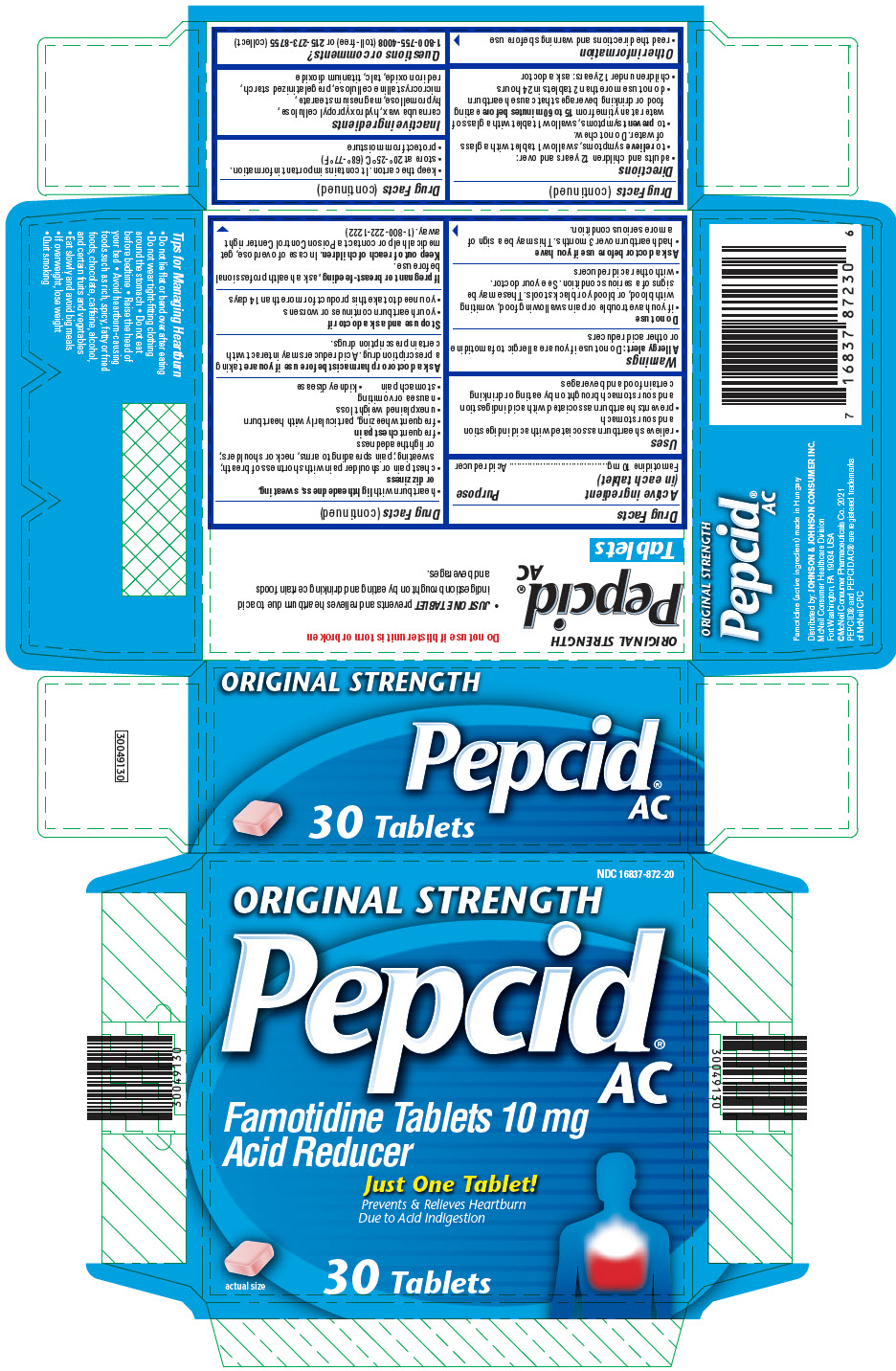 DRUG LABEL: Pepcid AC
NDC: 16837-872 | Form: TABLET, FILM COATED
Manufacturer: Kenvue Brands LLC
Category: otc | Type: HUMAN OTC DRUG LABEL
Date: 20260206

ACTIVE INGREDIENTS: FAMOTIDINE 10 mg/1 1
INACTIVE INGREDIENTS: CARNAUBA WAX; HYDROXYPROPYL CELLULOSE, UNSPECIFIED; HYPROMELLOSE, UNSPECIFIED; MAGNESIUM STEARATE; MICROCRYSTALLINE CELLULOSE; FERRIC OXIDE RED; TALC; TITANIUM DIOXIDE

Pepcid AC
Original Strength

Drug Facts

Active ingredient (in each tablet)

Famotidine 10 mg

Purpose

Acid reducer

Uses

- relieves heartburn associated with acid indigestion and sour stomach
- prevents heartburn associated with acid indigestion and sour stomach brought on by eating or drinking certain food and beverages

Warnings

Allergy alert

Do not use if you are allergic to famotidine or other acid reducers

Do not use

- if you have trouble or pain swallowing food, vomiting with blood, or bloody or black stools. These may be signs of a serious condition. See your doctor.
- with other acid reducers

Ask a doctor before use if you have

- had heartburn over 3 months. This may be a sign of a more serious condition.
- heartburn with lightheadedness, sweating, or dizziness
- chest pain or shoulder pain with shortness of breath; sweating; pain spreading to arms, neck or shoulders; or lightheadedness
- frequent chest pain
- frequent wheezing, particularly with heartburn
- unexplained weight loss
- nausea or vomiting
- stomach pain
- kidney disease

Ask a doctor or pharmacist before use if you are taking a prescription drug. Acid reducers may interact with certain prescription drugs.

Stop use and ask a doctor if

- your heartburn continues or worsens
- you need to take this product for more than 14 days

PREGNANCY OR BREAST FEEDING

If pregnant or breast-feeding, ask a health professional before use.

Keep out of reach of children. In case of overdose, get medical help or contact a Poison Control Center right away. (1-800-222-1222)

Directions

- adults and children 12 years and over:
  - to relieve symptoms, swallow 1 tablet with a glass of water. Do not chew.
  - to prevent symptoms, swallow 1 tablet with a glass of water at any time from 15 to 60 minutes before eating food or drinking beverages that cause heartburn
  - do not use more than 2 tablets in 24 hours
- children under 12 years: ask a doctor

Other information

- read the directions and warnings before use
- keep the carton. It contains important information.
- store at 20°-25°C (68°-77°F)
- protect from moisture

Inactive ingredients

carnauba wax, hydroxypropyl cellulose, hypromellose, magnesium stearate, microcrystalline cellulose, pregelatinized starch, red iron oxide, talc, titanium dioxide

Questions or comments?

1-800-755-4008 (toll-free) or 215-273-8755 (collect)

PRINCIPAL DISPLAY PANEL

NDC 16837-872-20

ORIGINAL STRENGTH

Pepcid®
AC

Famotidine Tablets 10 mg
Acid Reducer

Just One Tablet!
Prevents & Relieves Heartburn
Due to Acid Indigestion

actual size

30 Tablets